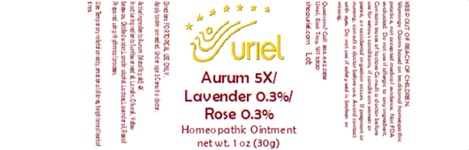 DRUG LABEL: Aurum 5X Lavender 0.3 Rose 0.3
NDC: 48951-1398 | Form: OINTMENT
Manufacturer: Uriel Pharmacy, Inc
Category: homeopathic | Type: HUMAN OTC DRUG LABEL
Date: 20250221

ACTIVE INGREDIENTS: GOLD 4 [hp_X]/1 g
INACTIVE INGREDIENTS: LAVENDER OIL; LANOLIN; SUNFLOWER OIL; OLIVE OIL; LACTOSE; ROSE OIL; WATER; BEESWAX; LANOLIN ALCOHOLS

Aurum 5X Lavender 0.3 Rose 0.3

INDICATIONS AND USAGE

Directions: FOR TOPICAL USE ONLY.

DOSAGE AND ADMINISTRATION

Apply to skin as needed. Under age 2: Consult a doctor.

Active Ingredients: Aurum (Metallic gold) 4X

INACTIVE INGREDIENT

Inactive Ingredients: Sunflower seed oil, Lanolin, Olive oil, Yellow beeswax, Distilled water,Lanolin alcohol, Lactose, Lavender oil, Rose oil
Prepared using rhythmical processes.

PURPOSE

Uses: Temporary relief of anxiety, emotional distress, heightened levels of stress.

KEEP OUT OF REACH OF CHILDREN.

WARNINGS

Warnings: Claims based on traditional homeopathic practice, not accepted medical evidence. Not FDA evaluated. Do not use if allergic to any ingredient. Contains traces of lactose Consult a doctor before use for serious conditions, if conditions worsen or persist, or accidental ingestion occurs. If pregnant or nursing, consult a doctor before use. Avoid contact with eyes. Do not use if safety seal is broken or missing.

Questions? Call 866.642.2858
Uriel, East Troy, WI 53120
shopuriel.com Lot: